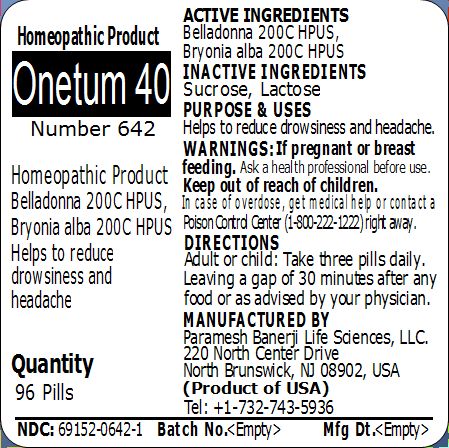 DRUG LABEL: Onetum 40 Number 642
NDC: 69152-0642 | Form: PELLET
Manufacturer: Paramesh Banerji Life Sciences LLC
Category: homeopathic | Type: HUMAN OTC DRUG LABEL
Date: 20150325

ACTIVE INGREDIENTS: ATROPA BELLADONNA 200 [hp_C]/1 1; BRYONIA ALBA ROOT 200 [hp_C]/1 1
INACTIVE INGREDIENTS: SUCROSE; LACTOSE

Active Ingredients

Belladonna 200C HPUS, Bryonia alba 200C HPUS

Inactive Ingredients

Sucrose, Lactose

Purpose

Helps to reduce drowsiness and headache

Uses

Helps to reduce drowsiness and headache

Warnings

If pregnant or breast feeding ask a health professional before use.

Keep out of reach of children. In case of overdose, get medical help or contact a Poison Control Center (1-800-222-1222) right away.

Direction

Adult or child: Take three pills daily. Leaving a gap of 30 minutes after any food or as advised by your physician.

Manufactured by

Paramesh Banerji Life Sciences, LLC

220 North Center Drive

North Brunswick, NJ 08902, USA

Product of USA

Tel: +1-732-743-5936

Principal Display Panel

Homeopathic Product

Onetum 40

Number 642

Homeopathic Product

Belladonna 200C HPUS, Bryonia alba 200C HPUS

Helps to reduce drowsiness and headache

Quantity

96 Pills